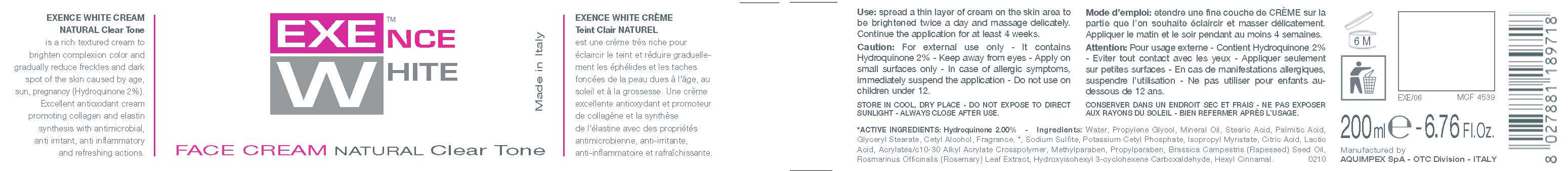 DRUG LABEL: EXENCE WHITE
NDC: 66273-0001 | Form: CREAM
Manufacturer: AQUIMPEX SPA
Category: otc | Type: HUMAN OTC DRUG LABEL
Date: 20110712

ACTIVE INGREDIENTS: HYDROQUINONE 4 mL/200 mL
INACTIVE INGREDIENTS: WATER; ROSEMARY; METHYLPARABEN; PROPYLENE GLYCOL; CETYL ALCOHOL; STEARIC ACID; PALMITIC ACID; CARBOMER 934; GLYCERYL MONOSTEARATE; ISOPROPYL MYRISTATE; MINERAL OIL; POTASSIUM CETYL PHOSPHATE; PROPYLPARABEN; CITRIC ACID MONOHYDRATE; LACTIC ACID; SODIUM SULFITE; BRASSICA RAPA VAR. RAPA OIL

Exence White Face Cream Natural Clear Tone

Natural Clear Tone - Lightening

EXENCE WHITE CREAM NATURAL Clear Tone is a rich textured cream to brighten complexion color and gradually reduce freckles and dark spot of the skin caused by age, sun, pregnancy.
Excellent antioxidant cream promoting collagen and elastin synthesis with antimicrobial, anti irritant, anti inflammatory and refreshing actions.

Use

Use: spread a thin layer of cream on the skin area to be brightened twice a day and massage delicately. Continue the application for at least 4 weeks.

Caution

Caution: For external use only - It contains Hydroquinone 2% - Keep away from eyes - Apply on small surfaces only - In case of allergic symptoms, immediately suspend the application - Do not use on children under 12.

Active Ingredients

ACTIVE INGREDIENTS: Hydroquinone 2.00%

Ingredients

Ingredients: Water, Propylene Glycol, Mineral Oil, Stearic Acid, Palmitic Acid,Glyceryl Stearate, Cetyl Alcohol, Fragrance, *, Sodium Sulfite, Potassium Cetyl Phosphate, Isopropyl Myristate, Citric Acid, Lactic Acid, Acrylates/c10-30 Alkyl Acrylate Crosspolymer, Methylparaben, Propylparaben, Brassica Campestris (Rapeseed) Seed Oil, Rosmarinus Officinalis (Rosemary) Leaf Extract, Hydroxyisohexyl 3-cyclohexene Carboxaldehyde, Hexyl Cinnamal.

STORAGE AND HANDLING

STORE IN COOL, DRY PLACE - DO NOT EXPOSE TO DIRECT SUNLIGHT - ALWAYS CLOSE AFTER USE.

Caution

Caution: For external use only - It contains Hydroquinone 2% - Keep away from eyes - Apply on small surfaces only - In case of allergic symptoms, immediately suspend the application - Do not use on children under 12.

Use

Use: spread a thin layer of cream on the skin area to be brightened twice a day and massage delicately. Continue the application for at least 4 weeks.